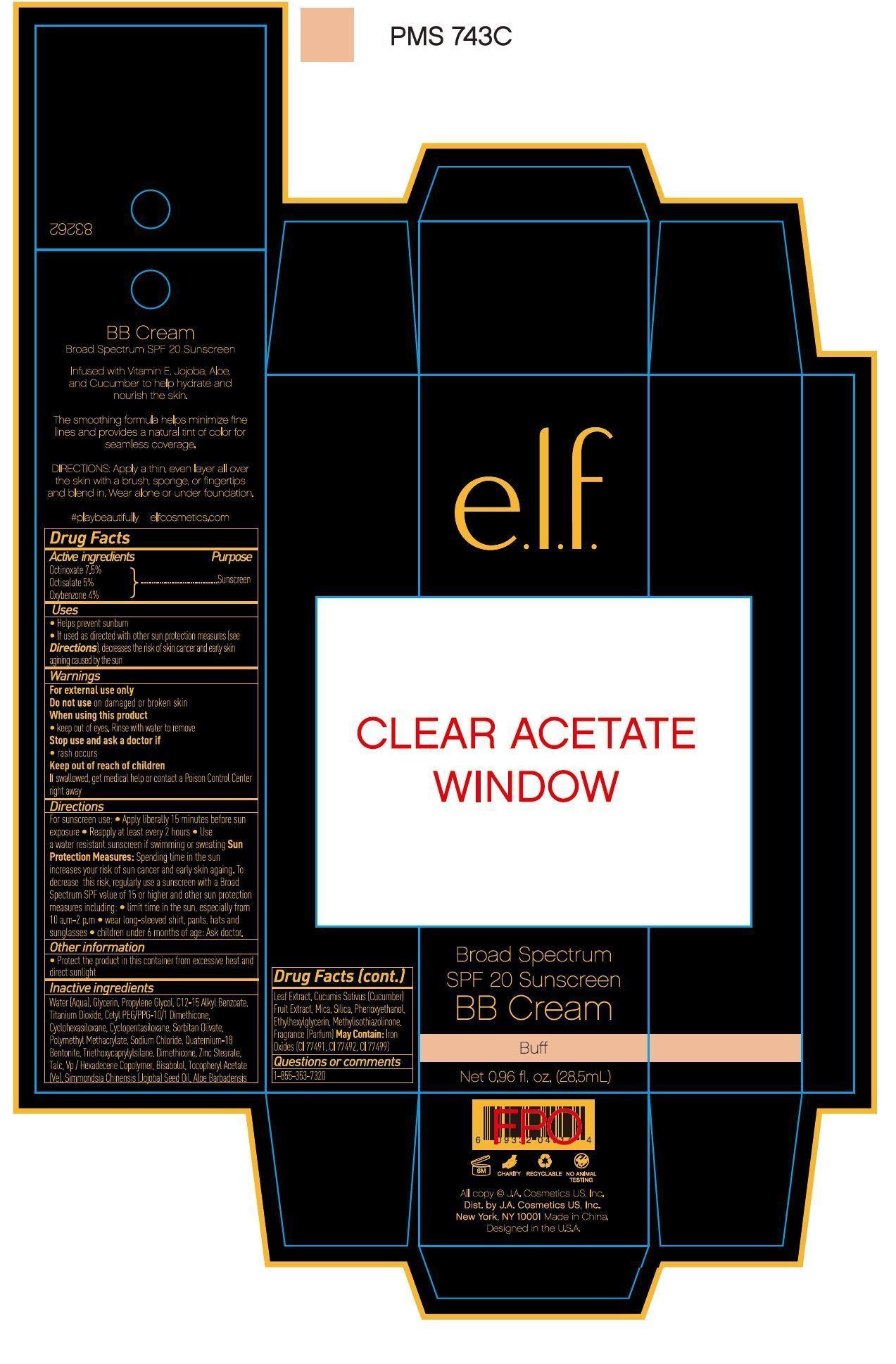 DRUG LABEL: ELF Broad Spectrum SPF 20 Sunscreen Buff BB Cream
NDC: 76354-610 | Form: CREAM
Manufacturer: J. A. Cosmetics U.S. INC
Category: otc | Type: HUMAN OTC DRUG LABEL
Date: 20151017

ACTIVE INGREDIENTS: OCTINOXATE 7.5 g/100 mL; OXYBENZONE 4 g/100 mL; OCTISALATE 5 g/100 mL
INACTIVE INGREDIENTS: WATER; SILICON DIOXIDE; MICA; GLYCERIN; PROPYLENE GLYCOL; ALKYL (C12-15) BENZOATE; FERRIC OXIDE RED; FERRIC OXIDE YELLOW; FERROSOFERRIC OXIDE; TITANIUM DIOXIDE; CETYL PEG/PPG-10/1 DIMETHICONE (HLB 2); SORBITAN OLIVATE; SODIUM CHLORATE; QUATERNIUM-18; BENTONITE; TRIETHOXYCAPRYLYLSILANE; DIMETHICONE; ZINC STEARATE; TALC; .ALPHA.-TOCOPHEROL ACETATE; ALOE ANDONGENSIS LEAF; JOJOBA OIL; CUCUMBER FRUIT OIL; PHENOXYETHANOL; ETHYLHEXYLGLYCERIN; METHYLISOTHIAZOLINONE

Drug Fact

Active Ingredient:

OCTINOXATE: 7.5%

OCTISALATE: 5.0%

OXYBENONE: 4.0%

Purpose:

Sunscreen

Uses:

Help prevent sunburn

If used as directed with other sun protection measures, decreases the risk of skin cancer and early skin aging caused by the sun

Warning:

For external use only

Do not use on damaged or broken skin

When using this product:

Keep out of eyes. Rinse with water to remove.

Stop Use and Ask a Doctor if:

Rash occurs

Keep Out of Reach of Children

If swallowed, get medical help or contact a poison control center immediately

Directions:

For sunscreen use:

Apply generously 15 min before sun exposure. Reapply every two hours.

Use a water resistant sunscreen if swimming or sweating

Sun Protection Measures:

Spending time in sun increases your risk of skin cancer or early skin aging. To decrease the risk, regularly use a sunscreen with broad spectrum SPF value of 15 or higher and other sun protection measures including

- Limit time in the sun, especially from 10 am to 2 pm
- Wear long sleeved shirts, pants, hats, and sunglasses.
- Children under six months of age: ask a doctor

Inactive Ingredient:

Water, Glycerin, Propylene Glycol, C12-15 Akyl Benzoate, Titanium Dioxide, Cetyl PEG/PPG-10/1 Dimethicone, Cyclohexasiloxane, Cyclopentasiloxane, Sorbitan Olivate, Polymethyl Methacrylate, Sodium Chloride, Quaternium-18, Bentonite, Triethoxycaprylsilane, Dimethicone, Zinc Stereate, Talc, VP/Hexadecene Copolymer, Bisabolol, Tocopheryl Acetate, Simmondsia Chinensis (Jojoba) Seed Oil, Aloe Barbadensis Leaf Extract, Cucumis Sativus (Cucumber) Fruit Extract, Mica, Silica, Phenoxyethanol, Ethylhexylglycerin, Methylisothiazolinone, Fragrance

May contain:

Iron Oxides (CI 77491, CI 77492, CI 77499)